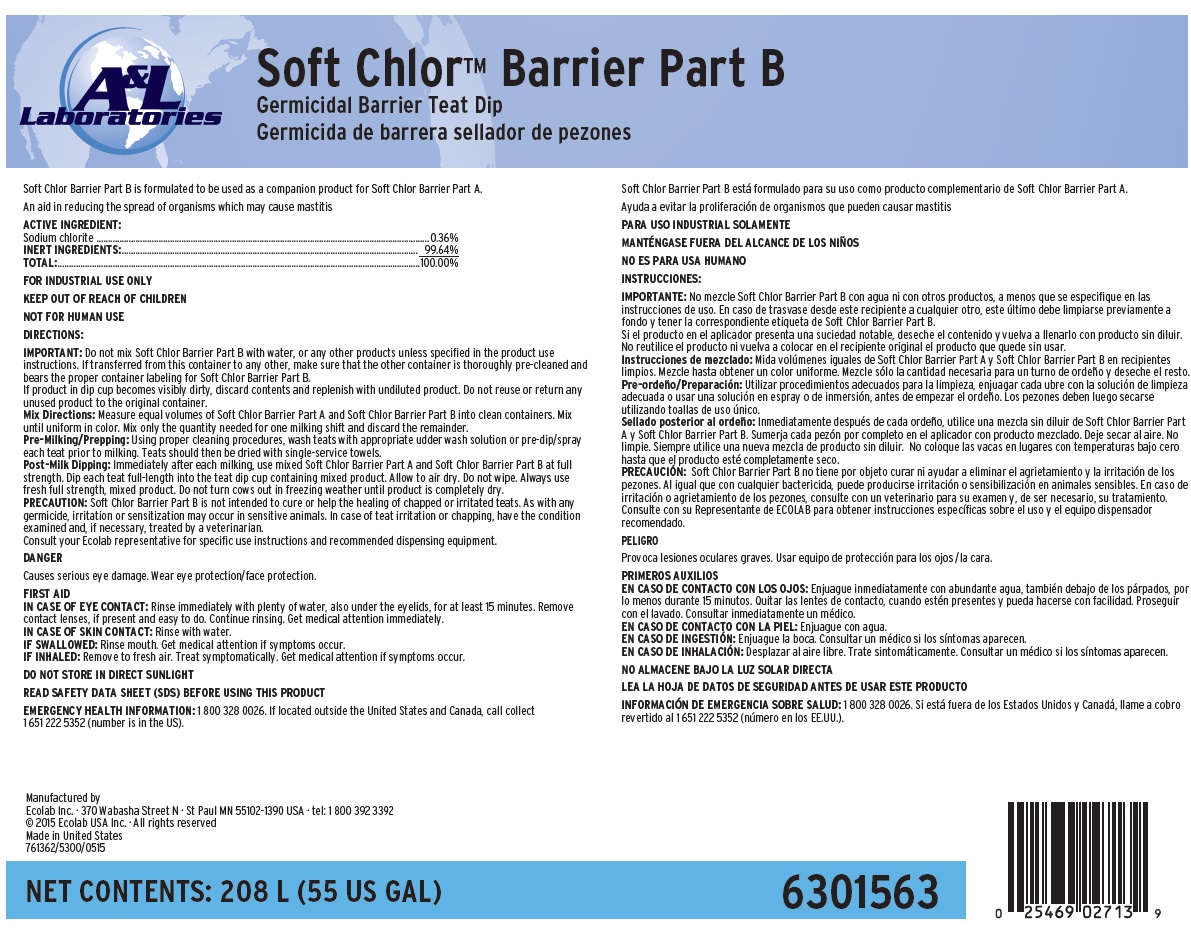 DRUG LABEL: Soft Chlor Barrier Part B
NDC: 47593-608 | Form: SOLUTION
Manufacturer: Ecolab Inc.
Category: animal | Type: OTC ANIMAL DRUG LABEL
Date: 20251118

ACTIVE INGREDIENTS: SODIUM CHLORITE 3.6 mg/1 mL
INACTIVE INGREDIENTS: WATER

SAFE HANDLING WARNING

FOR INDUSTRIAL USE ONLY

KEEP OUT OF REACH OF CHILDREN

NOT FOR HUMAN USE

DANGER

Causes serious eye damage. Wear eye protection/face protection.

DIRECTIONS:

IMPORTANT: Do not mix Soft Chlor Barrier Part B with water, or any other products unless specified in the product use instructions. If transferred from this container to any other, make sure that the other container is thoroughly pre-cleaned and bears the proper container labeling for Soft Chlor Barrier Part B.

If product in dip cup becomes visibly dirty, discard contents and replenish with undiluted product. Do not reuse or return any unused product to the original container.

Mix Directions: Measure equal volumes of Soft Chlor Barrier Part A and Soft Chlor Barrier Part B into clean containers. Mix until uniform in color. Mix only the quantity needed for one milking shift and discard the remainder.

Pre-Milking/Prepping: Using proper cleaning procedures, wash teats with appropriate udder wash solution or pre-dip/spray each teat prior to milking. Teats should then be dried with single-service towels.

Post-Milk Dipping: Immediately after each milking, use mixed Soft Chlor Barrier Part A and Soft Chlor Barrier Part B at full strength. Dip each teat full-length into the teat dip cup containing mixed product. Allow to air dry. Do not wipe. Always use fresh full strength, mixed product. Do not turn cows out in freezing weather until product is completely dry.

PRECAUTION: Soft Chlor Barrier Part B is not intended to cure or help the healing of chapped or irritated teats. As with any germicide, irritation or sensitization may occur in sensitive animals. In case of teat irritation or chapping, have the condition examined and, if necessary, treated by a veterinarian.

Consult your Ecolab representative for specific use instructions and recommended dispensing equipment.

OTHER SAFETY INFORMATION

FIRST AID

IN CASE OF EYE CONTACT: Rinse immediately with plenty of water, also under the eyelids, for at least 15 minutes. Remove contact lenses, if present and easy to do. Continue rinsing. Get medical attention immediately.

IN CASE OF SKIN CONTACT: Rinse with water.

IF SWALLOWED: Rinse mouth. Get medical attention if symptoms occur.

IF INHALED: Remove to fresh air. Treat symptomatically. Get medical attention if symptoms occur.

DO NOT STORE IN DIRECT SUNLIGHT

READ SAFETY DATA SHEET (SDS) BEFORE USING THIS PRODUCT

EMERGENCY HEALTH INFORMATION: 1 800 328 0026. If located outside the United States and Canada, call collect 1 651 222 5352 (number is in the US).

Principal display panel and representative label

A&L Laboratories

Soft Chlor™ Barrier Part B

Germicidal Barrier Teat Dip

Soft Chlor Barrier Part B is formulated to be used as a companion product for Soft Chlor Barrier Part A. An aid in reducing the spread of organisms which may cause mastitis

ACTIVE INGREDIENT:

Sodium chlorite........................................0.36%

INERT INGREDIENTS:............................... 99.64%

TOTAL:....................................................100.00%

Manufactured by

Ecolab Inc. · 370 Wabasha Street N · St Paul MN 55102-1390 USA · tel: 1 800 392 3392

© 2015 Ecolab USA Inc. · All rights reserved

Made in United States

761362/5300/0515

NET CONTENTS: 208 L (55 US GAL) 6301563